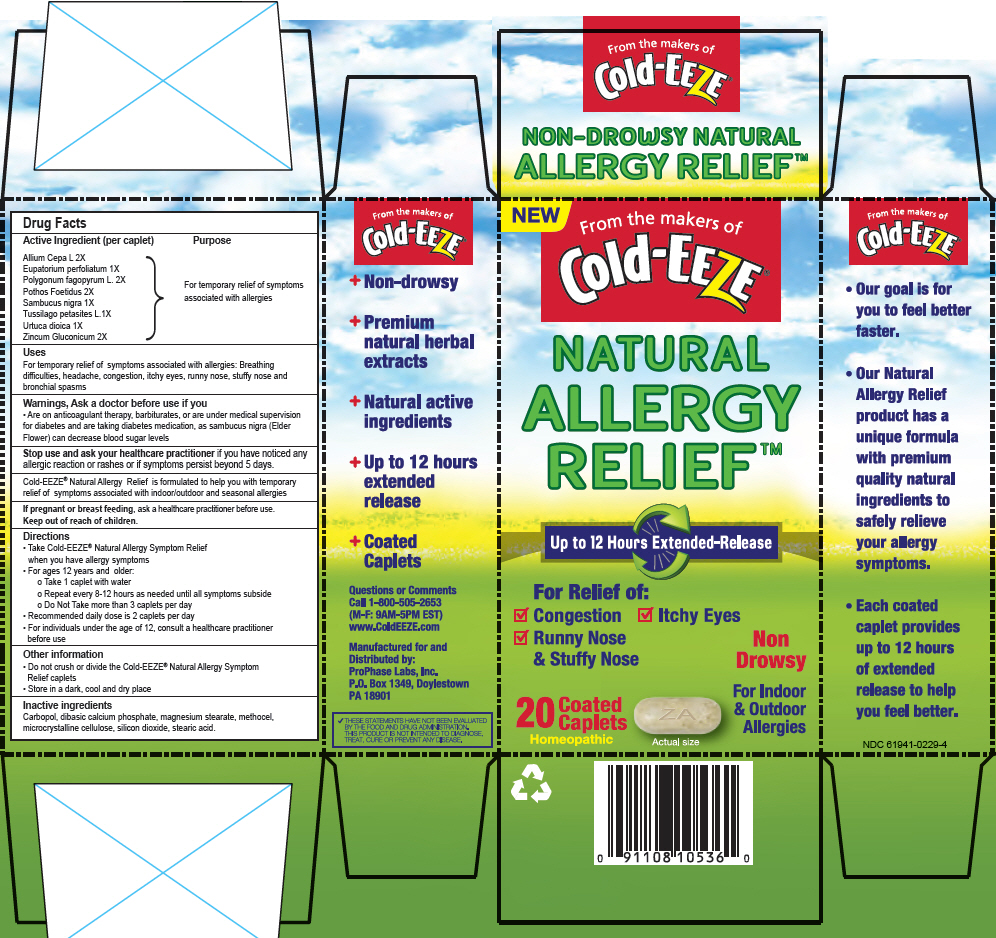 DRUG LABEL: Cold-EEZE 
NDC: 61941-0229 | Form: TABLET, DELAYED RELEASE
Manufacturer: ProPhase Labs, Inc.
Category: homeopathic | Type: HUMAN OTC DRUG LABEL
Date: 20160128

ACTIVE INGREDIENTS: Onion 2 [hp_X]/1 1; Eupatorium Perfoliatum Flowering Top 1 [hp_X]/1 1; Buckwheat 2 [hp_X]/1 1; Symplocarpus Foetidus Root 2 [hp_X]/1 1; Sambucus Nigra Flower 1 [hp_X]/1 1; Tussilago Farfara Leaf 1 [hp_X]/1 1; Urtica Dioica 1 [hp_X]/1 1; Zinc Gluconate 2 [hp_X]/1 1
INACTIVE INGREDIENTS: Carbomer Homopolymer Type C (Allyl Pentaerythritol Crosslinked); Calcium Phosphate, Dibasic, Dihydrate; MAGNESIUM STEARATE; Methylcellulose (25 MPA.S); CELLULOSE, MICROCRYSTALLINE; SILICON DIOXIDE; Stearic Acid

Cold-EEZE®
Natural Allergy Relief™

Drug Facts

Active Ingredient (per caplet)

Allium Cepa L 2X
Eupatorium perfoliatum 1X
Polygonum fagopyrum L. 2X
Pothos Foetidus 2X
Sambucus nigra 1X
Tussilago petasites L.1X
Urtuca dioica 1X
Zincum Gluconicum 2X

Purpose

For temporary relief of symptoms associated with allergies

Uses

For temporary relief of symptoms associated with allergies: Breathing difficulties, headache, congestion, itchy eyes, runny nose, stuffy nose and bronchial spasms

Warnings

Ask a doctor before use if you

- Are on anticoagulant therapy, barbiturates, or are under medical supervision for diabetes and are taking diabetes medication, as sambucus nigra (Elder Flower) can decrease blood sugar levels

Stop use and ask your healthcare practitioner if you have noticed any allergic reaction or rashes or if symptoms persist beyond 5 days.

Cold-EEZE® Natural Allergy Relief is formulated to help you with temporary relief of symptoms associated with indoor/outdoor and seasonal allergies

PREGNANCY OR BREAST FEEDING

If pregnant or breast feeding, ask a healthcare practitioner before use.

Keep out of reach of children.

Directions

- Take Cold-EEZE® Natural Allergy Symptom Relief when you have allergy symptoms
- For ages 12 years and older:
  - Take 1 caplet with water
  - Repeat every 8-12 hours as needed until all symptoms subside
  - Do Not Take more than 3 caplets per day
- Recommended daily dose is 2 caplets per day
- For individuals under the age of 12, consult a healthcare practitioner before use

Other information

- Do not crush or divide the Cold-EEZE® Natural Allergy Symptom Relief caplets
- Store in a dark, cool and dry place

Inactive ingredients

Carbopol, dibasic calcium phosphate, magnesium stearate, methocel, microcrystalline cellulose, silicon dioxide, stearic acid.

Questions or Comments

Call 1-800-505-2653 (M-F: 9AM-5PM EST) www.ColdEEZE.com

Distributed by:
ProPhase Labs, Inc.
P.O. Box 1349, Doylestown
PA 18901

PRINCIPAL DISPLAY PANEL - 20 Caplet Blister Pack Box

NEW

From the makers of
Cold-EEZE®

NATURAL
ALLERGY
RELIEF™

Up to 12 Hours Extended-Release

For Relief of:

☑ Congestion
☑ Itchy Eyes
☑ Runny Nose
  & Stuffy Nose

Non
Drowsy

20
Coated
Caplets

Homeopathic

Actual size

For Indoor
& Outdoor
Allergies